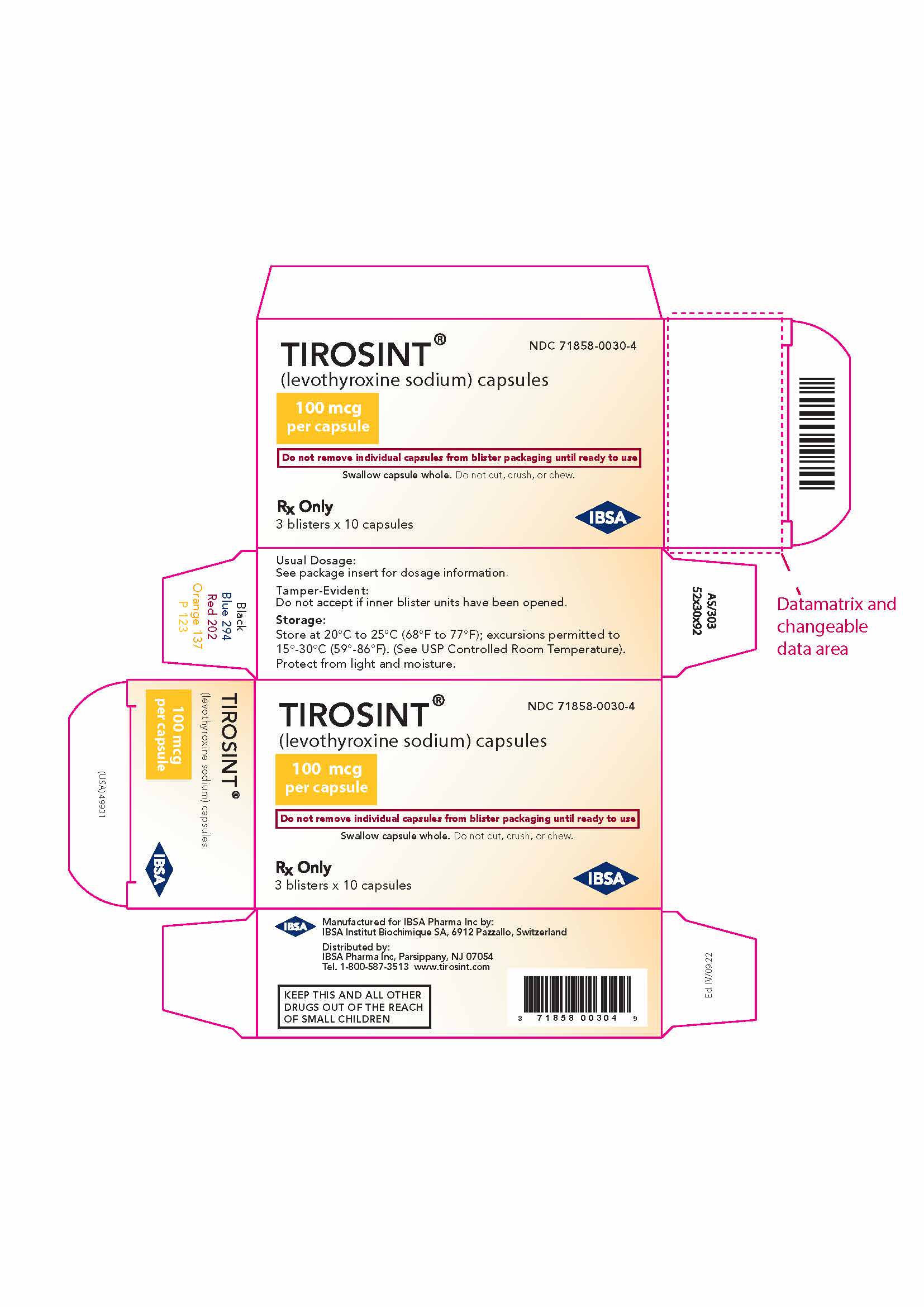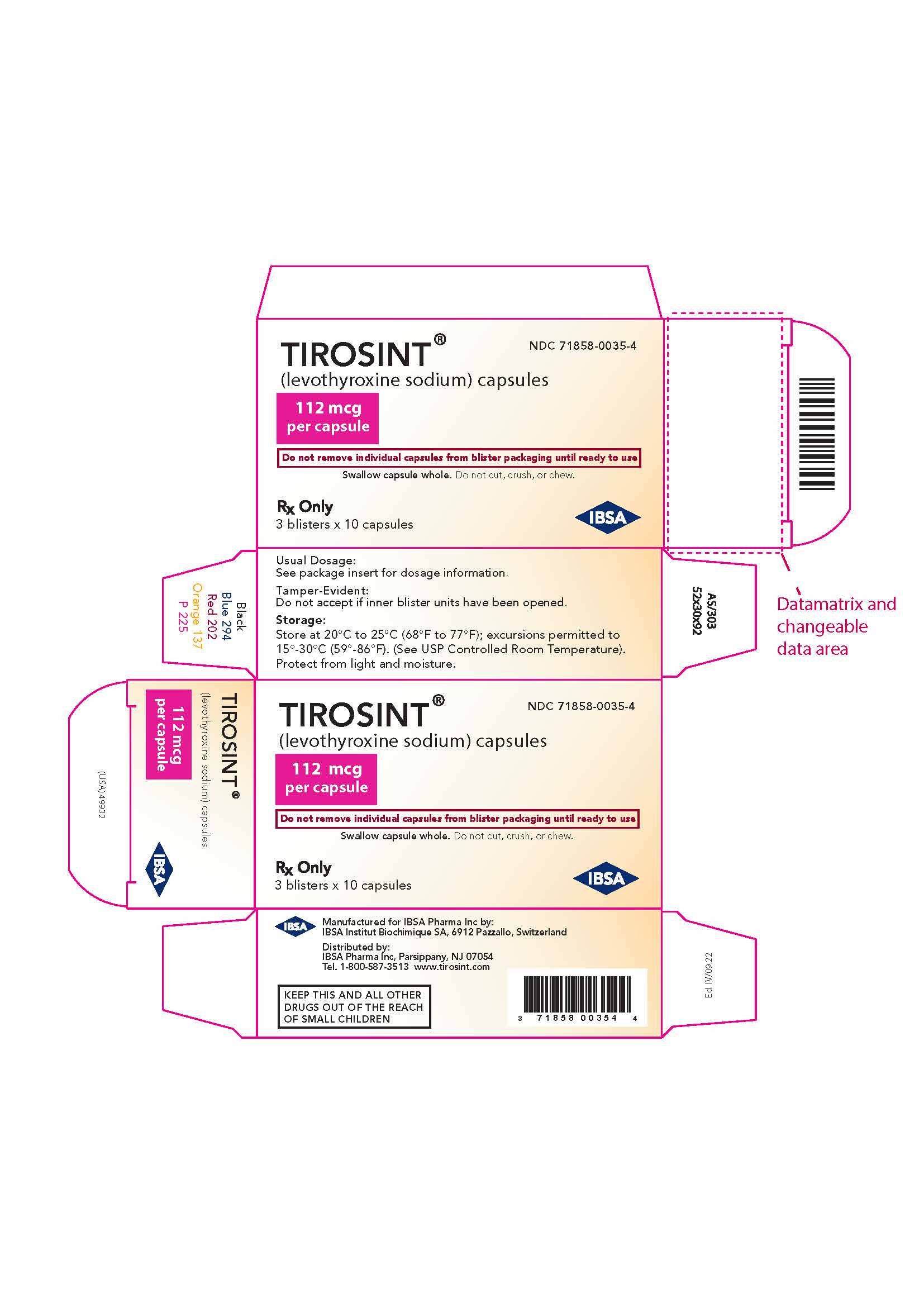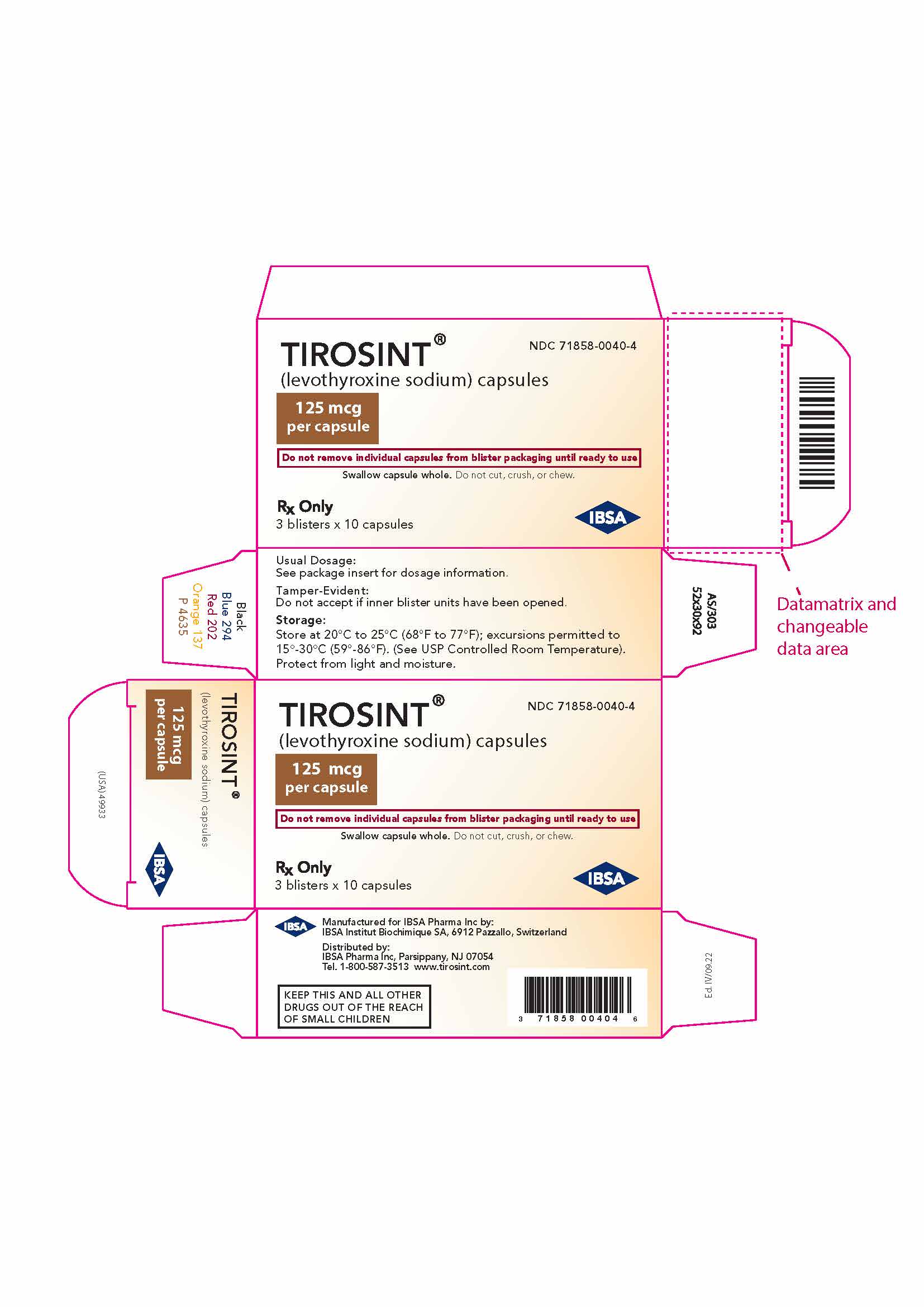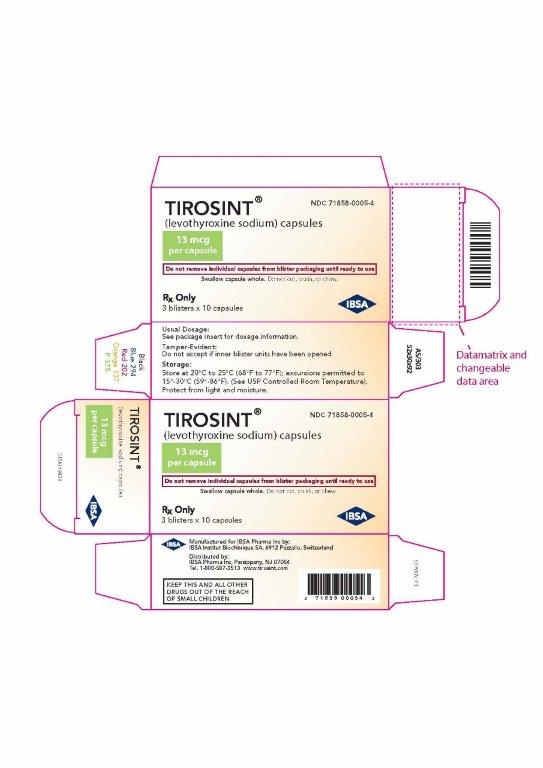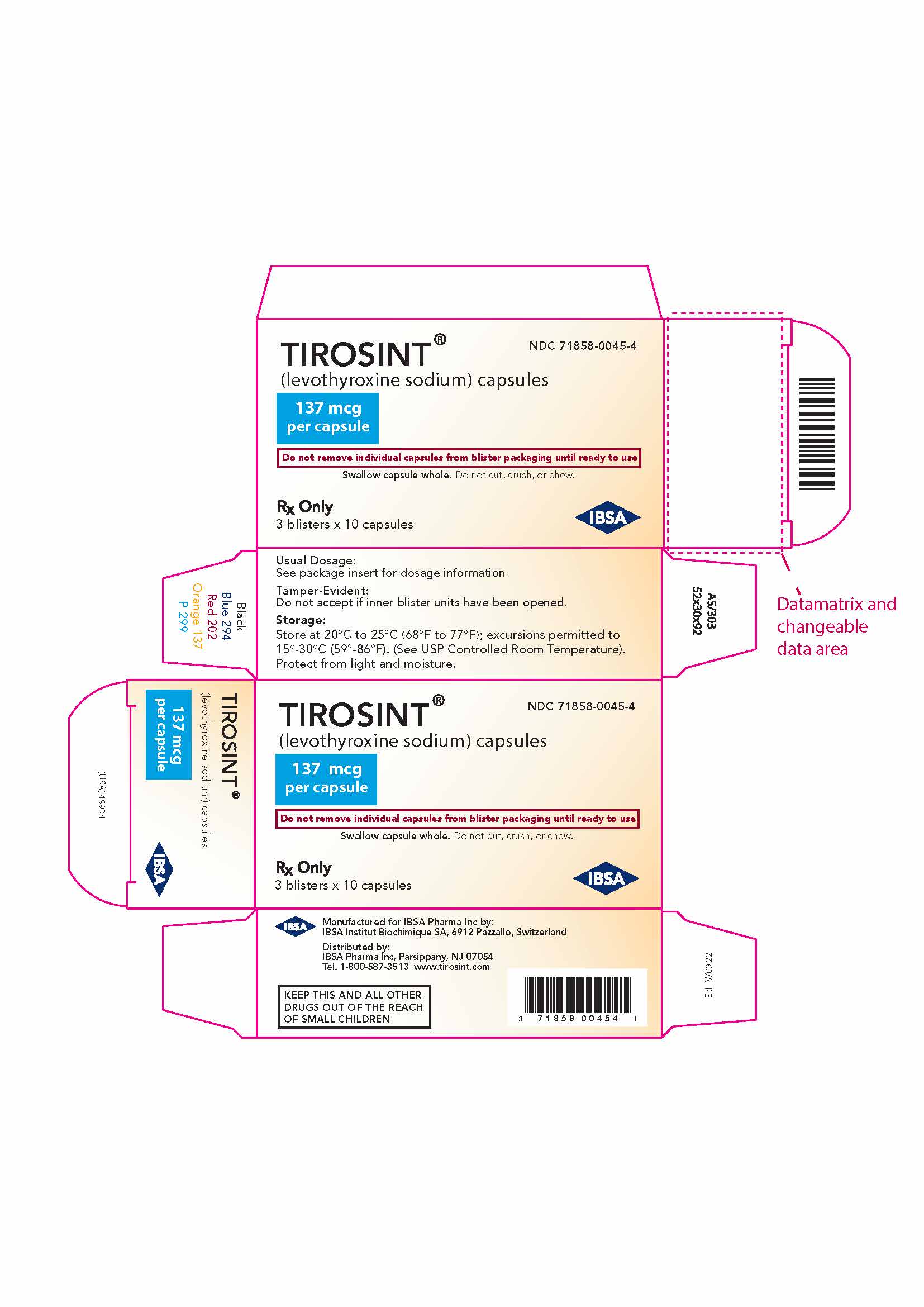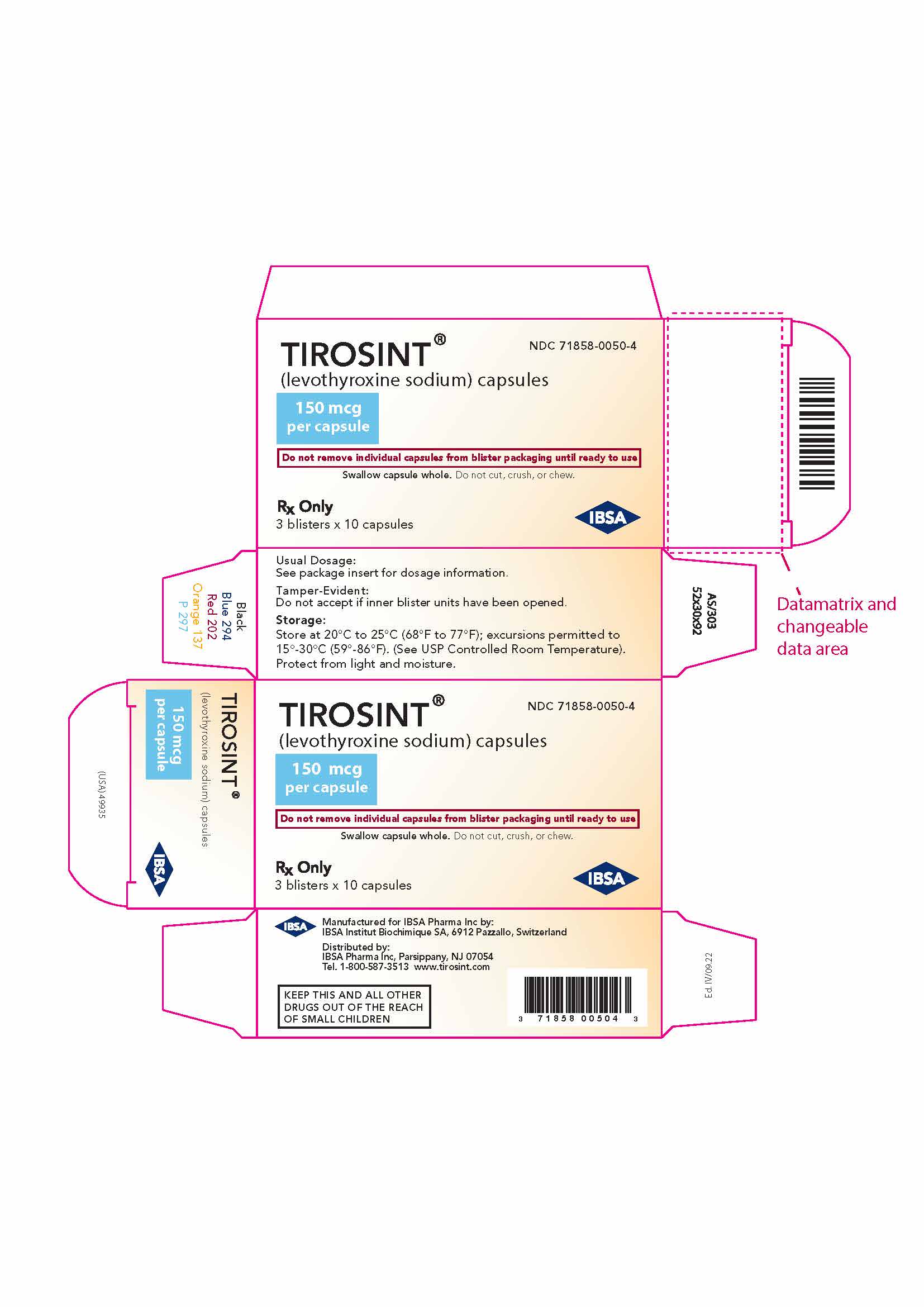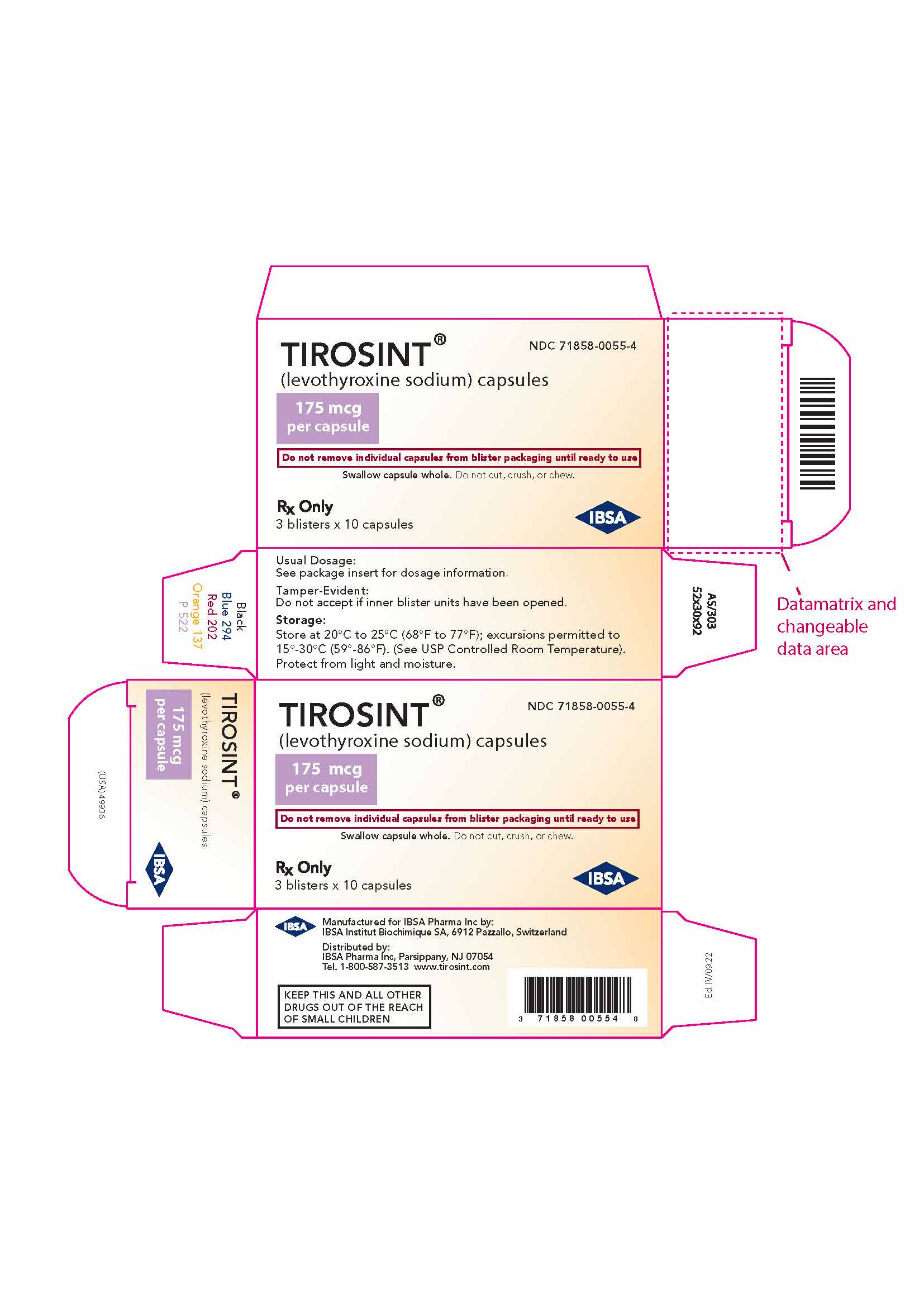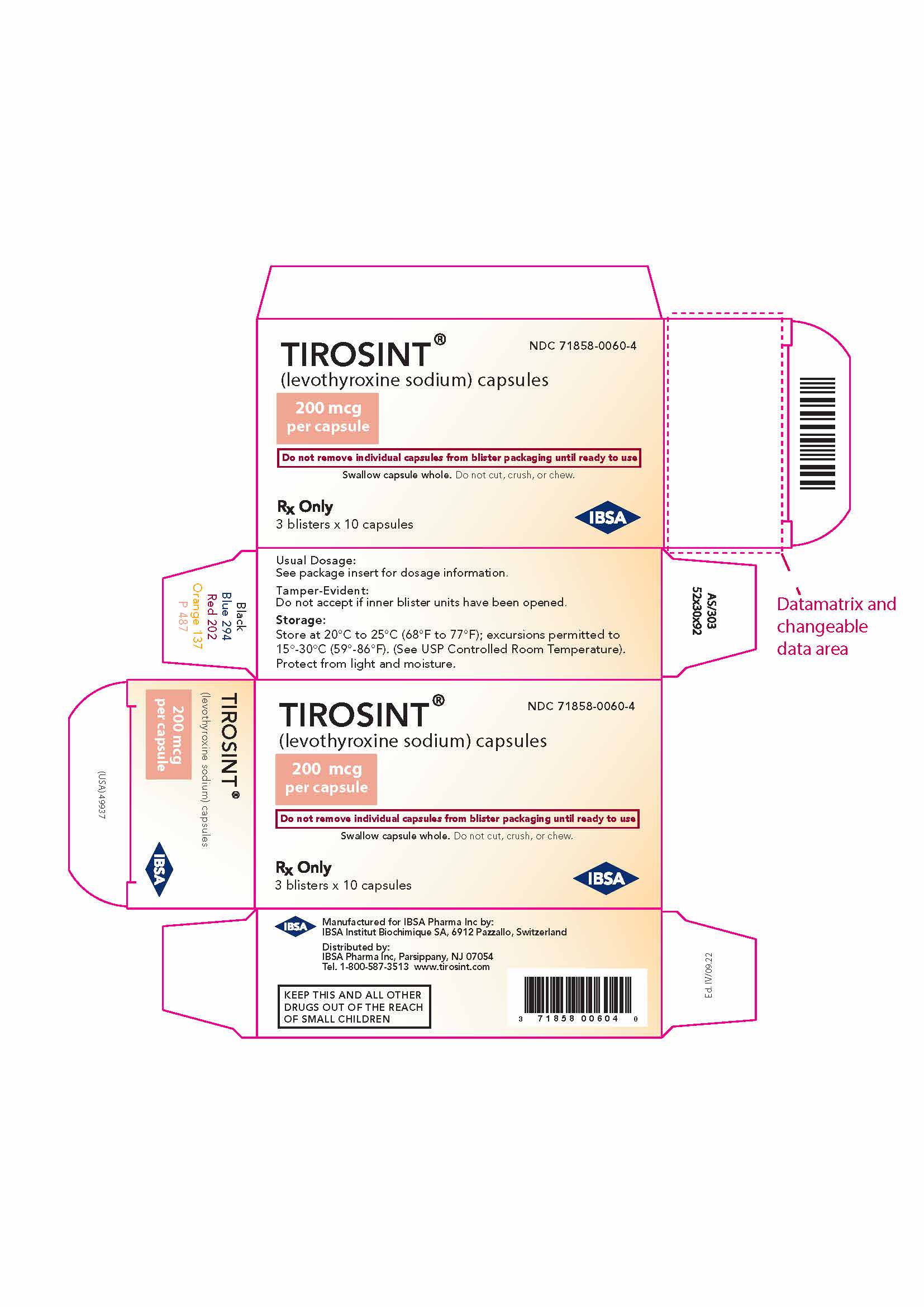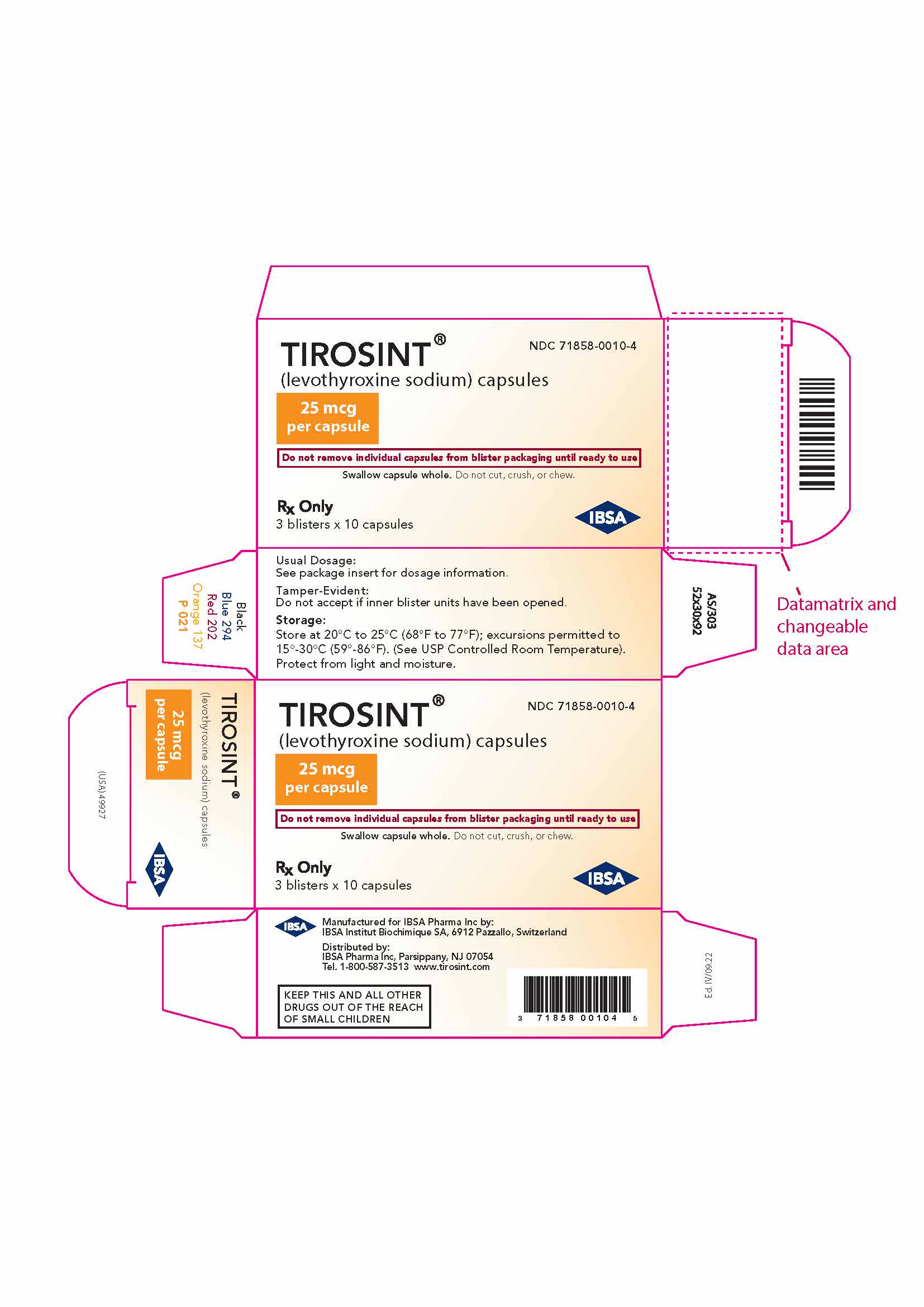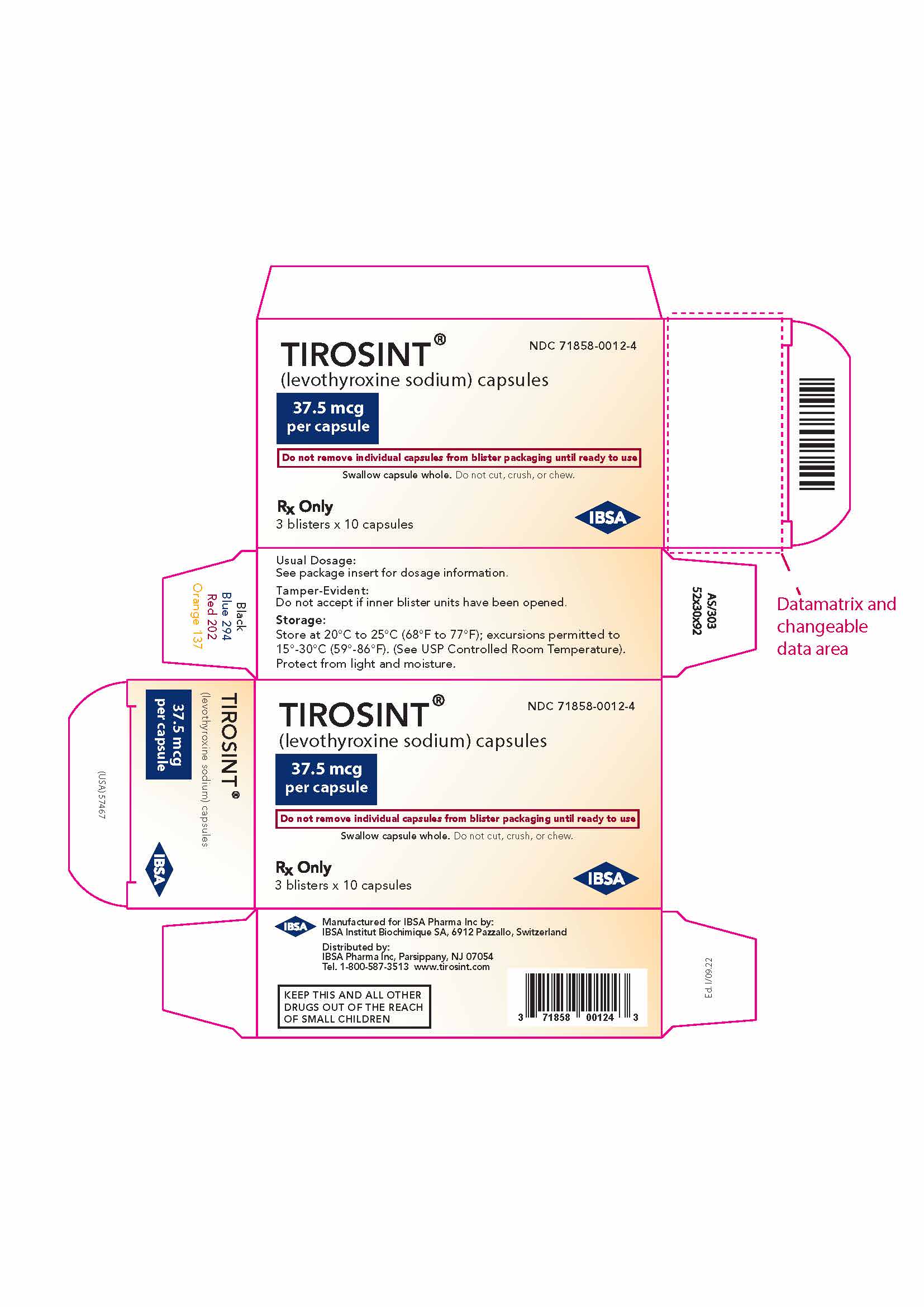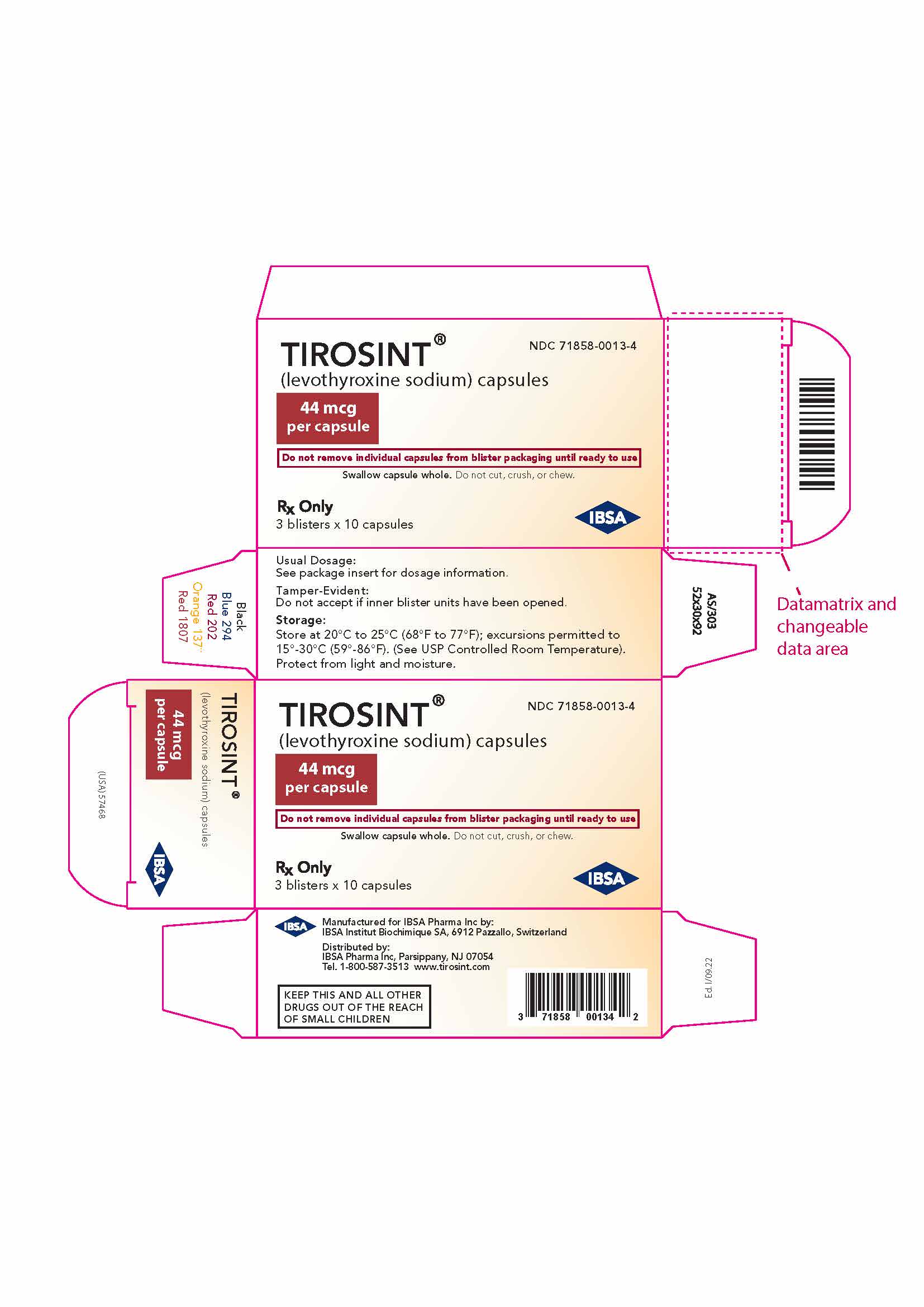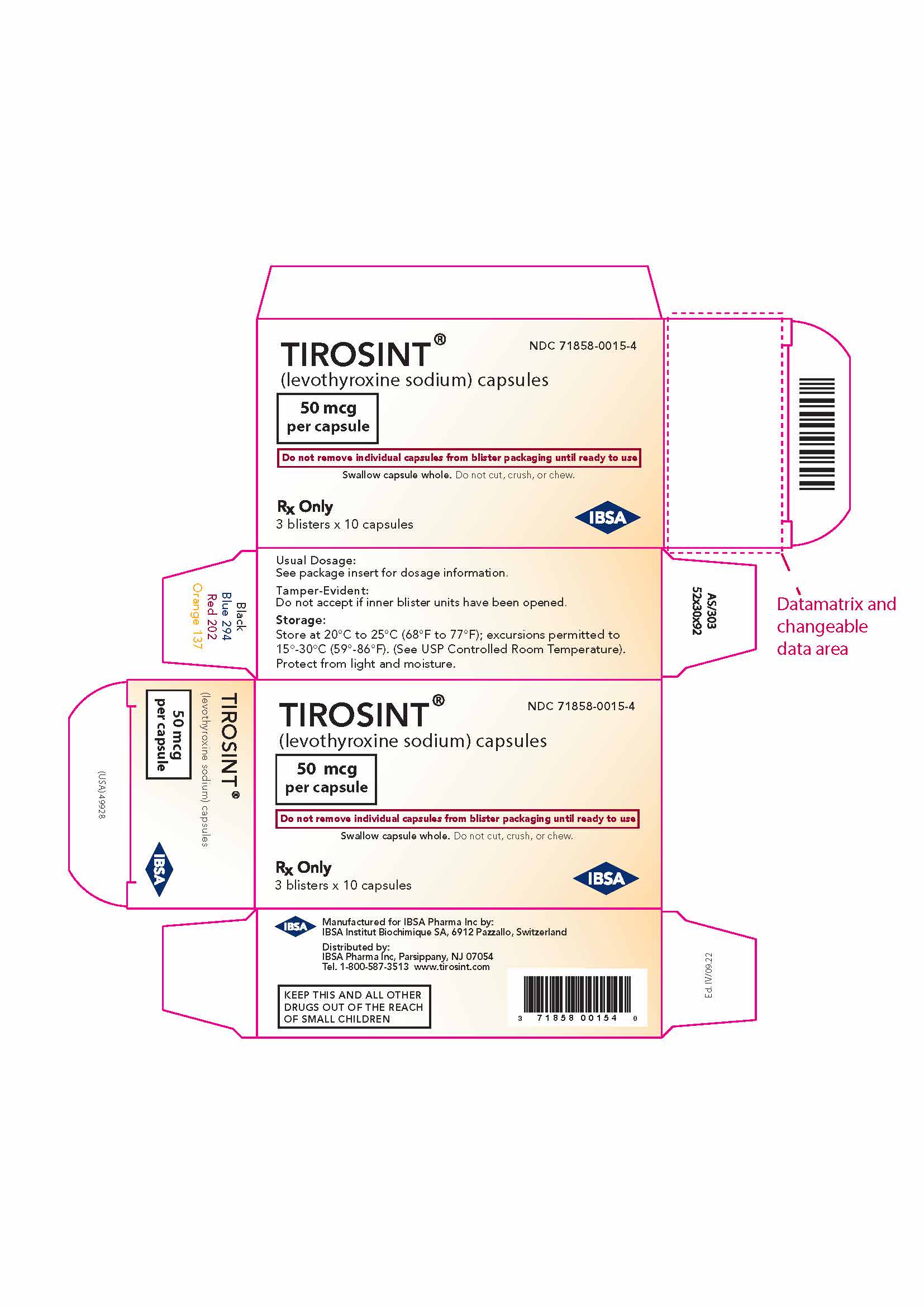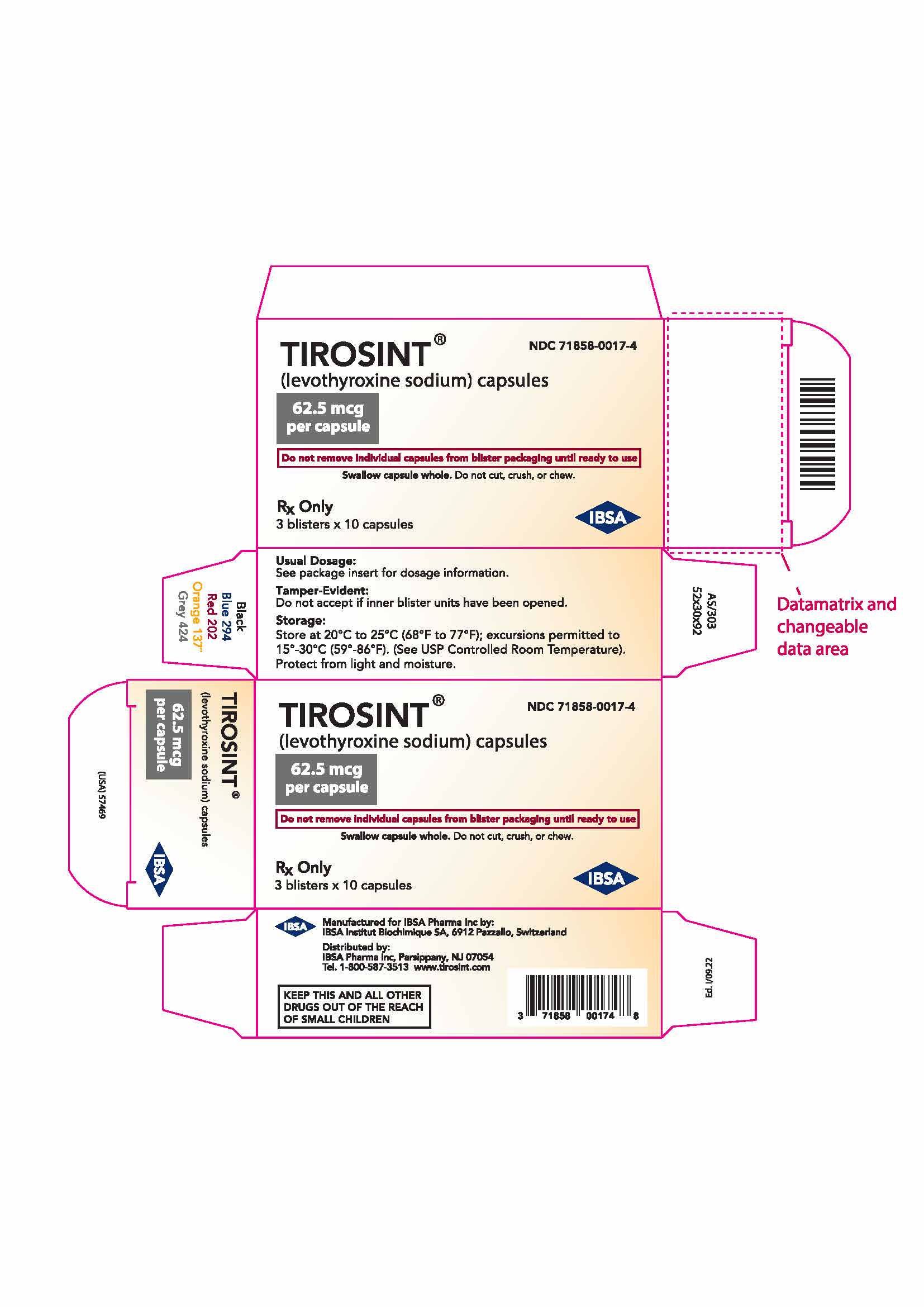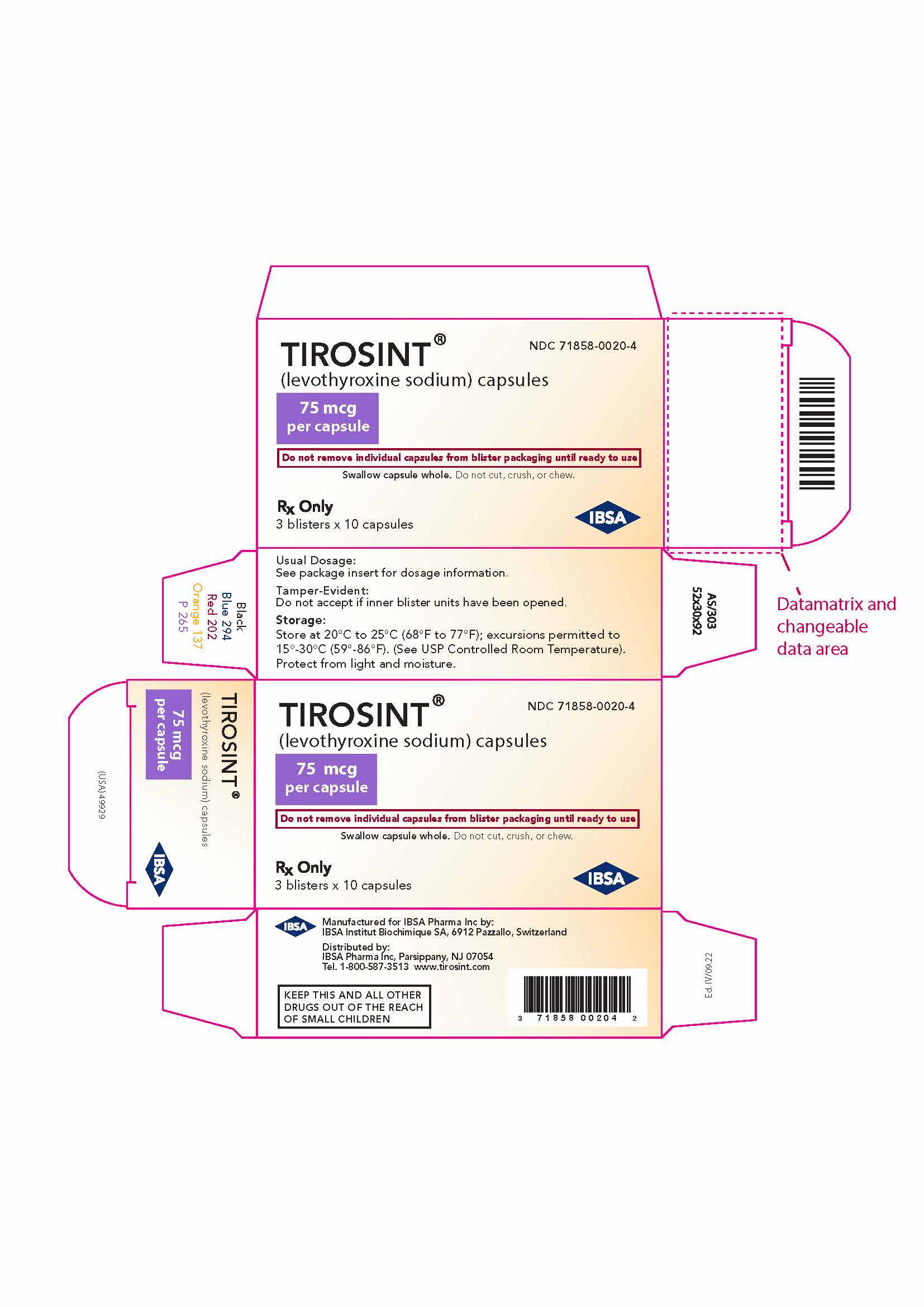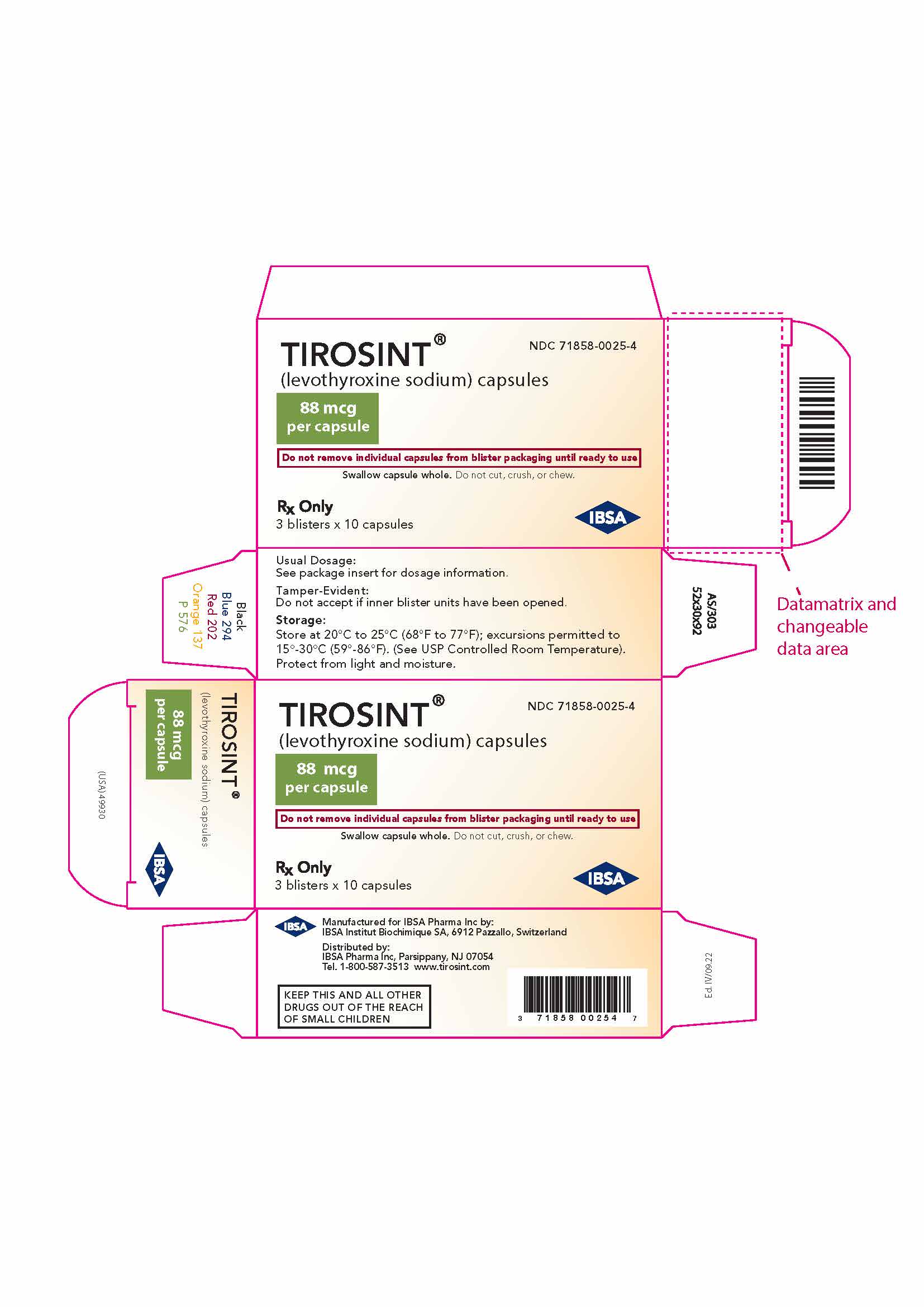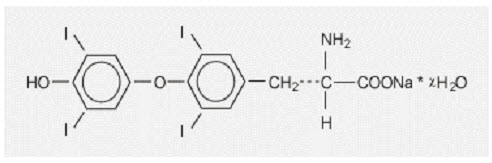 DRUG LABEL: Tirosint
NDC: 71858-0013 | Form: CAPSULE
Manufacturer: IBSA Pharma Inc.
Category: prescription | Type: HUMAN PRESCRIPTION DRUG LABEL
Date: 20250805

ACTIVE INGREDIENTS: LEVOTHYROXINE SODIUM 44 ug/1 1
INACTIVE INGREDIENTS: GLYCERIN; GELATIN, UNSPECIFIED; WATER

HIGHLIGHTS OF PRESCRIBING INFORMATION

These highlights do not include all the information needed to use TIROSINT® safely and effectively. See full prescribing information for TIROSINT.
TIROSINT® (levothyroxine sodium) capsules, for oral use
Initial U.S. Approval: 2000

WARNING: NOT FOR TREATMENT OF OBESITY or FOR WEIGHT LOSS

See full prescribing information for complete boxed warning

- Thyroid hormones, including TIROSINT, should not be used for the treatment of obesity or for weight loss.
- Doses beyond the range of daily hormonal requirements may produce serious or even life threatening manifestations of toxicity (6, 10).

1 INDICATION AND USAGE

TIROSINT is L-thyroxine (T4) indicated for adults and pediatric patients 6 years and older with:

- Hypothyroidism - As replacement therapy in primary (thyroidal), secondary (pituitary), and tertiary (hypothalamic) congenital or acquired hypothyroidism (1)
- Pituitary Thyrotropin (Thyroid-Stimulating Hormone, TSH) Suppression - As an adjunct to surgery and radioiodine therapy in the management of thyrotropin-dependent well-differentiated thyroid cancer (1)

Limitations of Use:

- Not indicated for suppression of benign thyroid nodules and nontoxic diffuse goiter in iodine-sufficient patients (1)
- Not indicated for treatment of transient hypothyroidism during the recovery phase of subacute thyroiditis (1)

2 DOSAGE AND ADMINISTRATION

- Administer once daily, on an empty stomach, one-half to one hour before breakfast (2.1)
- Administer at least 4 hours before or after drugs that are known to interfere with absorption (2.1)
- Evaluate the need for dose adjustments when regularly administering within an hour of certain foods that may affect TIROSINT absorption (2.1)
- Swallow TIROSINT capsules whole, do not cut, crush, or chew (2.1)
- Starting dose depends on a variety of factors, including age, body weight, cardiovascular status, concomitant medical conditions (including pregnancy), concomitant medications, co-administered food, and the specific nature of the condition being treated. Peak therapeutic effect may not be attained for 4-6 weeks (2.2)
- See full prescribing information for dosing in specific patient populations (2.3)
- Adequacy of therapy determined with periodic monitoring of TSH and/or T4 as well as clinical status (2.4)

3 DOSAGE FORMS AND STRENGTHS

Capsules: 13, 25, 37.5, 44, 50, 62.5, 75, 88, 100, 112, 125, 137, 150, 175, 200 mcg (3)

4 CONTRAINDICATIONS

- Uncorrected adrenal insufficiency (4)

5 WARNINGS AND PRECAUTIONS

- Cardiac adverse reactions in the elderly and in patients with underlying cardiovascular disease: Initiate TIROSINT at less than the full replacement dose because of the increased risk of cardiac adverse reactions, including atrial fibrillation. (2.3, 5.1, 8.5)
- Myxedema coma: Do not use oral thyroid hormone drug products to treat myxedema coma. (5.2)
- Acute adrenal crisis in patients with concomitant adrenal insufficiency: Treat with replacement glucocorticoids prior to initiation of TIROSINT treatment. (5.3)
- Prevention of hyperthyroidism or incomplete treatment of hypothyroidism: Proper dose titration and careful monitoring is critical to prevent the persistence of hypothyroidism or the development of hyperthyroidism. (5.4)
- Worsening of diabetic control: Therapy in patients with diabetes mellitus may worsen glycemic control and result in increased antidiabetic agent or insulin requirements. Carefully monitor glycemic control after starting, changing, or discontinuing thyroid hormone therapy. (5.5)
- Decreased bone mineral density associated with thyroid hormone over-replacement: Over-replacement can increase bone resorption and decrease bone mineral density. Give the lowest effective dose. (5.6)

6 ADVERSE REACTIONS

Adverse reactions associated with TIROSINT are primarily those of hyperthyroidism due to therapeutic overdosage including: arrhythmias, myocardial infarction, dyspnea, muscle spasm, headache, nervousness, irritability, insomnia, tremors, muscle weakness, increased appetite, weight loss, diarrhea, heat intolerance, menstrual irregularities, and skin rash (6)

To report SUSPECTED ADVERSE REACTIONS, contact IBSA Pharma Inc. at 1-800-587-3513, or FDA at 1-800-FDA-1088 or www.fda.gov/medwatch .

7 DRUG INTERACTIONS

See full prescribing information for drugs that affect thyroid hormone pharmacokinetics and metabolism (e.g., absorption, synthesis, secretion, catabolism, protein binding, and target tissue response) and may alter the therapeutic response to TIROSINT (7)

8 USE IN SPECIFIC POPULATIONS

Pregnancy may require the use of higher doses of TIROSINT (2.3, 8.1)

FULL PRESCRIBING INFORMATION

WARNING: NOT FOR TREATMENT OF OBESITY or FOR WEIGHT LOSS

- Thyroid hormones, including TIROSINT, either alone or with other therapeutic agents, should not be used for the treatment of obesity or for weight loss.
- In euthyroid patients, doses within the range of daily hormonal requirements are ineffective for weight reduction.
- Larger doses may produce serious or even life threatening manifestations of toxicity, particularly when given in association with sympathomimetic amines such as those used for their anorectic effects [see Adverse Reactions (6), Drug Interactions (7.7), and Overdosage (10)].

1 INDICATION AND USAGE

Hypothyroidism

TIROSINT is indicated as a replacement therapy in adults and pediatric patients 6 years and older with primary (thyroidal), secondary (pituitary), and tertiary (hypothalamic) congenital or acquired hypothyroidism.

Pituitary Thyrotropin (Thyroid-Stimulating Hormone, TSH) Suppression

TIROSINT is indicated as an adjunct to surgery and radioiodine therapy in the management of adults and pediatric patients 6 years and older with thyrotropin-dependent well-differentiated thyroid cancer.

Limitations of Use:

- TIROSINT is not indicated for suppression of benign thyroid nodules and nontoxic diffuse goiter in iodine-sufficient patients as there are no clinical benefits and overtreatment with TIROSINT may induce hyperthyroidism [see Warnings and Precautions (5.4)].
- TIROSINT is not indicated for treatment of transient hypothyroidism during the recovery phase of subacute thyroiditis.

2 DOSAGE AND ADMINISTRATION

2.1 General Administration Information

Administer TIROSINT as a single daily oral dose, on an empty stomach, one-half to one hour before breakfast.

Administer TIROSINT at least 4 hours before or after drugs known to interfere with TIROSINT absorption [see Drug Interactions (7.1)]

Evaluate the need for dose adjustments when regularly administering within an hour of certain foods that may affect TIROSINT absorption [see Drug Interactions (7.9) and Clinical Pharmacology (12.3)].

Swallow TIROSINT capsules whole, do not cut, crush, or chew.

2.2 General Principles of Dosing

The dose of TIROSINT for hypothyroidism or pituitary TSH suppression depends on a variety of factors including the patient's age, body weight, cardiovascular status, concomitant medical conditions (including pregnancy), concomitant medications, co-administered food, and the specific nature of the condition being treated [see Dosage and Administration (2.3), Warnings and Precautions (5), and Drug Interactions (7)] . Dosing must be individualized to account for these factors and dose adjustments made based on periodic assessment of the patient's clinical response and laboratory parameters [see Dosage and Administration (2.4)].

The peak therapeutic effect of a given dose of TIROSINT may not be attained for 4 to 6 weeks.

2.3 Dosing In Specific Patient Populations

Primary Hypothyroidism in Adults and in Adolescents in Whom Growth and Puberty are Complete

Start TIROSINT at the full replacement dose in otherwise healthy, non-elderly individuals who have been hypothyroid for only a short time (such as a few months).The average full replacement dose of TIROSINT is approximately 1.6 mcg per kg per day (for example: 100-125 mcg per day for a 70 kg adult).

Adjust the dose by 12.5 to 25 mcg increments every 4 to 6 weeks until the patient is clinically euthyroid and the serum TSH returns to normal. Doses greater than 200 mcg per day are seldom required. An inadequate response to daily doses greater than 300 mcg per day is rare and may indicate poor compliance, malabsorption, drug interactions, or a combination of these factors.

For elderly patients or patients with underlying cardiovascular disease, start with a dose of 12.5 to 25 mcg per day. Increase the dose every 6 to 8 weeks, as needed, until the patient is clinically euthyroid and the serum TSH returns to normal. The full replacement dose of TIROSINT may be less than 1 mcg per kg per day in elderly patients.

In patients with severe longstanding hypothyroidism, start with a dose of 12.5 to 25 mcg per day. Adjust the dose in 12.5 to 25 mcg increments every 2 to 4 weeks until the patient is clinically euthyroid and the serum TSH level is normalized.

Secondary or Tertiary Hypothyroidism

Start TIROSINT at the full replacement dose in otherwise healthy, non-elderly individuals. Start with a lower dose in elderly patients with underlying cardiovascular disease or patients with severe longstanding hypothyroidism as described above. Serum TSH is not a reliable measure of TIROSINT dose adequacy in patients with secondary or tertiary hypothyroidism, and should not be used to monitor therapy. Use the serum free-T4 level to monitor adequacy of therapy in this patient population. Titrate TIROSINT dosing per above instructions until the patient is clinically euthyroid and the serum free-T4 level is restored to the upper half of the normal range.

Pediatric Dosage - Congenital or Acquired Hypothyroidism

Only administer TIROSINT to pediatric patients 6 years and older who are able to swallow an intact capsule .

The recommended daily dose of TIROSINT in pediatric patients with hypothyroidism is based on body weight and changes with age as described in Table 1. Start TIROSINT at the full daily dose in most pediatric patients. Start at a lower dose in children at risk for hyperactivity (see below). Monitor for clinical and laboratory response [see Dosage and Administration (2.4)] .

Table 1: TIROSINT Dosing Guidelines for Pediatric Hypothyroidism
Age | Daily Dose Per Kg Body Weight [The dose should be adjusted based on clinical response and laboratory parameters [see Dosage and Administration (2.4) and Use in Specific Populations (8.4)] .]
6-12 years | 4-5 mcg/kg/day
Greater than 12 years but growth and puberty incomplete | 2-3 mcg/kg/day
Growth and puberty complete | 1.6 mcg/kg/day

Children at risk for hyperactivity: To minimize the risk of hyperactivity in children, start at one-fourth the recommended full replacement dose, and increase on a weekly basis by one-fourth the full-recommended replacement dose until the full recommended replacement dose is reached.

Pregnancy

Preexisting Hypothyroidism: TIROSINT dose requirements may increase during pregnancy . Measure serum TSH and free-T4 as soon as pregnancy is confirmed and, at a minimum, during each trimester of pregnancy. In patients with primary hypothyroidism, maintain serum TSH in the trimester-specific reference range. For patients with serum TSH above the normal trimester specific range, increase the dose of TIROSINT by 12.5 to 25 mcg per day and measure TSH every four weeks until a stable TIROSINT dose is reached and serum TSH is within the normal trimester specific range. Reduce TIROSINT dosage to pre-pregnancy levels immediately after delivery and measure serum TSH levels 4 to 8 weeks postpartum to ensure the TIROSINT dose is appropriate.

New Onset Hypothyroidism: Normalize thyroid function as rapidly as possible. In patients with moderate to severe signs and symptoms of hypothyroidism, start TIROSINT at the full replacement dose (1.6 mcg per kg body weight per day). In patients with mild hypothyroidism (TSH < 10 mIU per Liter), start TIROSINT at 1.0 mcg per kg body weight per day. Evaluate serum TSH every 4 weeks and adjust TIROSINT dosage until serum TSH is within the normal trimester specific range [see Use in Specific Populations (8.1)].

TSH Suppression in Well-Differentiated Thyroid Cancer

Generally, TSH is suppressed to below 0.1 mIU per Liter, and this usually requires a TIROSINT dose of greater than 2 mcg per kg per day. However, in patients with high-risk tumors, the target level for TSH suppression may be lower.

2.4 Monitoring TSH and/or Thyroxine (T4) Levels

Assess the adequacy of therapy by periodic assessment of laboratory tests and clinical evaluation. Persistent clinical and laboratory evidence of hypothyroidism despite an apparent adequate replacement dose of TIROSINT may be evidence of inadequate absorption, poor compliance, drug interactions, or a combination of these factors.

Adults

In adult patients with primary hypothyroidism, monitor serum TSH levels after an interval of 6 to 8 weeks after any change in dose. In patients on a stable and appropriate replacement dose, evaluate clinical and biochemical response every 6 to 12 months and whenever there is a change in the patient's clinical status.

Pediatrics

In patients with congenital hypothyroidism, assess the adequacy of replacement therapy by measuring both serum TSH and total or free-T4. Monitor TSH and total or free-T4 in children is as follows: at 2 and 4 weeks after the initiation of treatment 2 weeks after any change in dosage, and then every 3 to 12 months thereafter following dose stabilization until growth is completed. Poor compliance or abnormal values may necessitate more frequent monitoring. Perform routine clinical examination, including assessment of mental and physical growth and development, and bone maturation at regular intervals.

While the general aim of therapy is to normalize the serum TSH level, TSH may not normalize in some patients due to in utero hypothyroidism causing a resetting of the pituitary-thyroid feedback. Failure of the serum T4 to increase into the upper half of the normal range within 2 weeks of initiation of TIROSINT therapy and/or of the serum TSH to decrease below 20 mIU per Liter within 4 weeks may indicate the child is not receiving adequate therapy. Assess compliance, dose of medication administered, and method of administration prior to increasing the dose of TIROSINT [see Warnings and Precautions (5.4) and Use in Specific Populations (8.4)] .

Secondary (Pituitary) and Tertiary (Hypothalamic) Hypothyroidism

Monitor serum free-T4 levels maintain in the upper half of the normal range in these patients.

3 DOSAGE FORMS AND STRENGTHS

TIROSINT capsules are amber-colored, round/biconvex capsules, imprinted with a dosage strength specific letter on one side and containing a viscous amber-colored liquid and are available as follows:

Strength (mcg) | Imprint Code
13 | A
25 | E
37.5 | O
44 | R
50 | G
62.5 | L
75 | H
88 | J
100 | K
112 | M
125 | N
137 | P
150 | S
175 | U
200 | Y

4 CONTRAINDICATIONS

TIROSINT is contraindicated in patients with uncorrected adrenal insufficiency [see Warnings and Precautions (5.3)].

5 WARNINGS AND PRECAUTIONS

5.1 Cardiac Adverse Reactions in the Elderly and in Patients with Underlying Cardiovascular Disease

Overtreatment with levothyroxine may cause an increase in heart rate, cardiac wall thickness, and cardiac contractility and may precipitate angina or arrhythmias, particularly in patients with cardiovascular disease and in elderly patients. Initiate TIROSINT therapy in this population at lower doses than those recommended in younger individuals or in patients without cardiac disease [see Dosage and Administration (2.3) and Use in Specific Populations (8.5)].

Monitor for cardiac arrhythmias during surgical procedures in patients with coronary artery disease receiving suppressive TIROSINT therapy. Monitor patients receiving concomitant TIROSINT and sympathomimetic agents for signs and symptoms of coronary insufficiency . If cardiac symptoms develop or worsen, reduce the TIROSINT dose or withhold it for one week and restart at a lower dose.

5.2 Myxedema Coma

Myxedema coma is a life-threatening emergency characterized by poor circulation and hypometabolism, and may result in unpredictable absorption of levothyroxine sodium from the gastrointestinal tract. Use of oral thyroid hormone drug products is not recommended to treat myxedema coma. Administer thyroid hormone products formulated for intravenous administration to treat myxedema coma.

5.3 Acute Adrenal Crisis in Patients with Concomitant Adrenal Insufficiency

Thyroid hormone increases metabolic clearance of glucocorticoids. Initiation of thyroid hormone therapy prior to initiating glucocorticoid therapy precipitate an acute adrenal crisis in patient with adrenal insufficiency. Treat patients with adrenal insufficiency with replacement glucocorticoids prior to initiating treatment with TIROSINT [see Contraindications (4)].

5.4 Prevention of Hyperthyroidism or Incomplete Treatment of Hypothyroidism

TIROSINT has a narrow therapeutic index. Over- or under-treatment with TIROSINT may have negative effects on growth and development, cardiovascular function, bone metabolism, reproductive function, cognitive function, emotional state, gastrointestinal function, and on glucose and lipid metabolism. Titrate the dose of TIROSINT carefully and monitor response to titration to avoid these effects [see Dosage and Administration (2.4)] . Monitor for the presence of drug or food interactions when using TIROSINT and adjust the dose as necessary [see Drug Interactions (7) and Clinical Pharmacology (12.3)].

5.5 Worsening of Diabetic Control

Addition of levothyroxine therapy in patients with diabetes mellitus may worsen glycemic control and result in increased antidiabetic agent or insulin requirements. Carefully monitor glycemic control after starting, changing, or discontinuing thyroid hormone therapy [see Drug Interactions (7.2)] .

5.6 Decreased Bone Mineral Density Associated with Thyroid Hormone Over-Replacement

Increased bone resorption and decreased bone mineral density may occur as a result of levothyroxine over-replacement, particularly in post-menopausal women. The increased bone resorption may be associated with increased serum levels and urinary excretion of calcium and phosphorous, elevations in bone alkaline phosphatase, and suppressed serum parathyroid hormone levels. Administer the minimum dose of TIROSINT that achieves the desired clinical and biochemical response to mitigate against this risk.

6 ADVERSE REACTIONS

Adverse reactions associated with TIROSINT therapy are primarily those of hyperthyroidism due to therapeutic overdosage [see Warnings and Precautions (5) and Overdosage (10)]. They include the following:

- General: fatigue, increased appetite, weight loss, heat intolerance, fever, excessive sweating
- Central nervous system: headache, hyperactivity, nervousness, anxiety, irritability, emotional lability, insomnia
- Musculoskeletal: tremors, muscle weakness, muscle spasm
- Cardiovascular: palpitations, tachycardia, arrhythmias, increased pulse and blood pressure, heart failure, angina, myocardial infarction, cardiac arrest
- Respiratory: dyspnea
- Gastrointestinal (GI): diarrhea, vomiting, abdominal cramps, elevations in liver function tests
- Dermatologic: hair loss, flushing, rash
- Endocrine: decreased bone mineral density
- Reproductive: menstrual irregularities, impaired fertility

Seizures have been reported rarely with the institution of levothyroxine therapy.

Adverse Reactions in Children

Pseudotumor cerebri and slipped capital femoral epiphysis have been reported in children receiving levothyroxine therapy. Overtreatment may result in craniosynostosis in infants and premature closure of the epiphyses in children with resultant compromised adult height.

Hypersensitivity Reactions

Hypersensitivity reactions to inactive ingredients have occurred in patients treated with thyroid hormone products. These include urticaria, pruritus, skin rash, flushing, angioedema, various GI symptoms (abdominal pain, nausea, vomiting and diarrhea), fever, arthralgia, serum sickness and wheezing. Hypersensitivity to levothyroxine itself is not known to occur.

7 DRUG INTERACTIONS

7.1 Drugs Known to Affect Thyroid Hormone Pharmacokinetics

Many drugs can exert effects thyroid hormone pharmacokinetics (e.g., absorption, synthesis, secretion, catabolism, protein binding, and target tissue response) and may alter the therapeutic response to TIROSINT (see Tables 2 to 5 below).

Table 2: Drugs That May Decrease T4 Absorption (Hypothyroidism)
Potential impact: Concurrent use may reduce the efficacy of TIROSINT by binding and delaying or preventing absorption, potentially resulting in hypothyroidism
Drug or Drug Class | Effect
Calcium Carbonate Ferrous Sulfate | Calcium carbonate may form an insoluble chelate with levothyroxine, and ferrous sulfate likely forms a ferric-thyroxine complex. Administer TIROSINT at least 4 hours apart from these agents.
Orlistat | Monitor patients treated concomitantly with orlistat and TIROSINT for changes in thyroid function.
Bile Acid Sequestrants -Colesevelam -Cholestyramine -Colestipol Ion Exchange Resins -Kayexalate -Sevelamer | Bile acid sequestrants and ion exchange resins are known to decrease levothyroxine absorption. Administer TIROSINT at least 4 hours prior to these drugs or monitor thyrotropin (TSH) levels.
Other drugs: Proton Pump Inhibitors Sucralfate Antacids - Aluminum & Magnesium Hydroxides - Simethicone | Gastric acidity is an essential requirement for adequate absorption of levothyroxine. Sucralfate, antacids and proton pump inhibitors may cause hypochlorhydria, affect intragastric pH, and reduce levothyroxine absorption. Monitor patients appropriately

Table 3: Drugs That May Alter T4 and Triiodothyronine (T3) Serum Transport Without Affecting Free Thyroxine (FT4) Concentration (Euthyroidism)
Drug or Drug Class | Effect
Clofibrate Estrogen-containing oral contraceptives Estrogens (oral) Heroin / Methadone 5-Fluorouracil Mitotane Tamoxifen | These drugs may increase serum thyroxine-binding globulin (TBG) concentration.
Androgens / Anabolic Steroids Asparaginase Glucocorticoids Slow-Release Nicotinic Acid | These drugs may decrease serum TBG concentration.
Potential impact (below) : Administration of these agents with TIROSINT results in an initial transient increase in FT4. Continued administration results in a decrease in serum T4 and normal FT4 and TSH concentrations.
Salicylates (> 2 g/day) | Salicylates inhibit binding of T4 and T3 to TBG and transthyretin. An initial increase in serum FT4 is followed by return of FT4 to normal levels with sustained therapeutic serum salicylate concentrations, although total T4 levels may decrease by as much as 30%.
Other drugs: Carbamazepine Furosemide (> 80 mg IV) Heparin Hydantoins Non-Steroidal Anti-inflammatory Drugs - Fenamates | These drugs may cause protein-binding site displacement . Furosemide has been shown to inhibit the protein binding of T4 to TBG and albumin, causing an increased free-T4 fraction in serum. Furosemide competes for T4-binding sites on TBG, prealbumin, and albumin, so that a single high dose can acutely lower the total T4 level. Phenytoin and carbamazepine reduce serum protein binding of levothyroxine, and total and free-T4 may be reduced by 20% to 40%, but most patients have normal serum TSH levels and are clinically euthyroid. Closely monitor thyroid hormone parameters.

Table 4: Drugs That May Alter Hepatic Metabolism of T4 (Hypothyroidism)
Potential impact: Stimulation of hepatic microsomal drug-metabolizing enzyme activity may cause increased hepatic degradation of levothyroxine, resulting in increased TIROSINT requirements.
Drug or Drug Class | Effect
Phenobarbital Rifampin | Phenobarbital has been shown to reduce the response to thyroxine. Phenobarbital increases L-thyroxine metabolism by inducing uridine 5'-diphospho-glucuronosyltransferase (UGT) and leads to a lower T4 serum levels. Changes in thyroid status may occur if barbiturates are added or withdrawn from patients being treated for hypothyroidism. Rifampin has been shown to accelerate the metabolism of levothyroxine.

Table 5: Drugs That May Decrease Conversion of T4 to T3
Potential impact: Administration of these enzyme inhibitors decreases the peripheral conversion of T4 to T3, leading to decreased T3 levels. However, serum T4 levels are usually normal but may occasionally be slightly increased.
Drug or Drug Class | Effect
Beta-adrenergic antagonists (e.g., Propranolol > 160 mg/day) | In patients treated with large doses of propranolol (> 160 mg/day), T3 and T4 levels change, TSH levels remain normal, and patients are clinically euthyroid. Actions of particular beta-adrenergic antagonists may be impaired when the hypothyroid patient is converted to the euthyroid state.
Glucocorticoids (e.g., Dexamethasone ≥ 4 mg/day) | Short-term administration of large doses of glucocorticoids may decrease serum T3 concentrations by 30% with minimal change in serum T4 levels. However, long-term glucocorticoid therapy may result in slightly decreased T3 and T4 levels due to decreased TBG production (see Table 3 above).
Other: Amiodarone | Amiodarone inhibits peripheral conversion of levothyroxine (T4) to triiodothyronine (T3) and may cause isolated biochemical changes (increase in serum free-T4, and decrease or normal free-T3) in clinically euthyroid patients.

7.2 Antidiabetic Therapy

Addition of TIROSINT therapy in patients with diabetes mellitus may worsen glycemic control and result in increased antidiabetic agent or insulin requirements. Careful monitor glycemic control, especially when thyroid therapy is started, changed, or discontinued [see Warnings and Precautions (5.5)] .

7.3 Oral Anticoagulants

TIROSINT increases the response to oral anticoagulant therapy. Therefore, a decrease in the dose of anticoagulant may be warranted with correction of the hypothyroid state or when the TIROSINT dose is increased. Closely monitor coagulation tests to permit appropriate and timely dosage adjustments.

7.4 Digitalis Glycosides

TIROSINT may reduce the therapeutic effects of digitalis glycosides. Serum digitalis glycoside levels may decrease when a hypothyroid patient becomes euthyroid, necessitating an increase in the dose of digitalis glycosides.

7.5 Antidepressant Therapy

Concurrent use of tricyclic (e.g., Amitriptyline) or tetracyclic (e.g., Maprotiline) antidepressants and TIROSINT may increase the therapeutic and toxic effects of both drugs, possibly due to increased receptor sensitivity to catecholamines. Toxic effects may include increased risk of cardiac arrhythmias and central nervous system stimulation. TIROSINT may accelerate the onset of action of tricyclics. Administration of sertraline in patients stabilized on TIROSINT may result in increased TIROSINT requirements.

7.6 Ketamine

Concurrent use of ketamine and TIROSINT may produce marked hypertension and tachycardia. Closely monitor blood pressure and heart rate in these patients.

7.7 Sympathomimetics

Concurrent use of sympathomimetics and TIROSINT may increase the effects of sympathomimetics or thyroid hormone. Thyroid hormones may increase the risk of coronary insufficiency when sympathomimetic agents are administered to patients with coronary artery disease.

7.8 Tyrosine-Kinase Inhibitors

Concurrent use of tyrosine-kinase inhibitors such as imatinib may cause hypothyroidism. Closely monitor TSH levels in such patients.

7.9 Drug-Food Interactions

Consumption of certain foods may affect TIROSINT absorption thereby necessitating adjustments in dosing [see Dosage and Administration (2.1)] . Soybean flour (infant formula), cottonseed meal, walnuts, and dietary fiber may bind and decrease the absorption of TIROSINT from the GI tract. Grapefruit juice may delay the absorption of levothyroxine and reduce its bioavailability.

7.10 Drug-Laboratory Test Interactions

Consider changes in TBG concentration when interpreting T4 and T3 values. Measure and evaluate unbound (free) hormone and/or determine the free T4 index (FT4I) in this circumstance. Pregnancy, infectious hepatitis, estrogens, estrogen-containing oral contraceptives, and acute intermittent porphyria increase TBG concentrations. Nephrosis, severe hypoproteinemia, severe liver disease, acromegaly, androgens and corticosteroids decrease TBG concentration. Familial hyper- or hypo-thyroxine binding globulinemias have been described, with the incidence of TBG deficiency approximating 1 in 9000.

8 USE IN SPECIFIC POPULATIONS

8.1 Pregnancy

Risk Summary

Experience with levothyroxine use in pregnant women, including data from post-marketing studies, have not reported increased rates of major birth defects or miscarriages [see Data]. There are risks to the mother and fetus associated with untreated hypothyroidism in pregnancy. Since thyroid-stimulating hormone (TSH) levels may increase during pregnancy, TSH should be monitored and TIROSINT dosage adjusted during pregnancy [see Clinical Considerations] . There are no animal studies conducted with levothyroxine during pregnancy. TIROSINT should not be discontinued during pregnancy and hypothyroidism diagnosed during pregnancy should be promptly treated.

The estimated background risk of major birth defects and miscarriage for the indicated population is unknown. In the U.S. general population, the estimated background risk of major birth defects and miscarriage in clinically recognized pregnancies is 2 to 4% and 15 to 20%, respectively.

Clinical Considerations

Disease-Associated Maternal and/or Embryo/Fetal Risk

Maternal hypothyroidism during pregnancy is associated with a higher rate of complications, including spontaneous abortion, gestational hypertension, pre-eclampsia, stillbirth, and premature delivery. Untreated maternal hypothyroidism may have an adverse effect on fetal neurocognitive development.

Dose Adjustments During Pregnancy and the Postpartum Period

Pregnancy may increase TIROSINT requirements. Serum TSH level should be monitored and the TIROSINT dosage adjusted during pregnancy. Since postpartum TSH levels are similar to preconception values, the TIROSINT dosage should return to the pre-pregnancy dose immediately after delivery [see Dosage and Administration (2.3)].

Data

Human Data

Levothyroxine is approved for use as a replacement therapy for hypothyroidism. There is a long experience of levothyroxine use in pregnant women, including data from post-marketing studies that have not reported increased rates of fetal malformations, miscarriages or other adverse maternal or fetal outcomes associated with levothyroxine use in pregnant women.

8.2 Lactation

Risk Summary

Limited published studies report that levothyroxine is present in human milk. However, there is insufficient information to determine the effects of levothyroxine on the breastfed infant and no available information on the effects of levothyroxine on milk production. Adequate levothyroxine treatment during lactation may normalize milk production in hypothyroid lactating mothers. The developmental and health benefits of breastfeeding should be considered along with the mother's clinical need for TIROSINT and any potential adverse effects on the breastfed infant from TIROSINT or from the underlying maternal condition.

8.4 Pediatric Use

TIROSINT is indicated for use in pediatric patients 6 years and older. The initial dose of TIROSINT varies with age and body weight. Dosing adjustments are based on an assessment of the individual patient's clinical and laboratory parameters [see Dosage and Administration (2.3, 2.4)]

In children in whom a diagnosis of permanent hypothyroidism has not been established, discontinue TIROSINT administration for a trial period. Obtain serum T4 and TSH levels at the end of the trial period, and use laboratory test results and clinical assessments to guide diagnosis and treatment, if warranted.

Congenital Hypothyroidism [see Dosage and Administration (2.3, 2.4)]

Rapid restoration of normal serum T4 concentrations is essential for preventing the adverse effects of congenital hypothyroidism on intellectual development as well as on overall physical growth and maturation. Therefore, initiate levothyroxine therapy immediately upon diagnosis. Levothyroxine is generally continued for life in these patients.

Closely monitor children during the first two weeks of TIROSINT therapy for cardiac overload and arrhythmias.

Closely monitor patients to avoid undertreatment and overtreatment. Undertreatment may have deleterious effects on intellectual development and linear growth. Overtreatment may adversely affect the tempo of brain maturation and accelerate the bone age with resultant premature closure of the epiphyses and compromised adult stature.

Acquired Hypothyroidism in Pediatric Patients

Closely monitor patients to avoid undertreatment and overtreatment. Undertreatment may result in poor school performance due to impaired concentration and slowed mentation and in reduced adult height. Overtreatment may accelerate the bone age and result in premature epiphyseal closure and compromised adult stature.

Treated children may manifest a period of catch-up growth, which may be adequate in some cases to normalize adult height. In children with severe or prolonged hypothyroidism, catch-up growth may not be adequate to normalize adult height.

8.5 Geriatric Use

Because of the increased prevalence of cardiovascular disease among the elderly, initiate TIROSINT therapy at less than the full replacement dose [ see Warnings and Precautions (5.1) and Dosage and Administration (2.3)]. Atrial arrhythmias can occur in elderly patients. Atrial fibrillation is the most common of the arrhythmias observed with levothyroxine overtreatment in the elderly .

10 OVERDOSAGE

The signs and symptoms of overdosage are those of hyperthyroidism [see Warnings and Precautions (5) and Adverse Reactions (6)]. In addition, confusion and disorientation may occur. Cerebral embolism, shock, coma, and death have been reported. Seizures occurred in a 3-year-old child ingesting 3.6 mg of levothyroxine. Symptoms may not necessarily be evident or may not appear until several days after ingestion of levothyroxine sodium.

Reduce the TIROSINT dose or discontinue temporarily if signs or symptoms of overdosage occur. Initiate appropriate supportive treatment as dictated by the patient's medical status.

For current information on the management of poisoning or overdosage, contact the National Poison Control Center at 1-800-222-1222 or www.poison.org.

11 DESCRIPTION

TIROSINT (levothyroxine sodium) capsules for oral use contain synthetic L-3,3',5,5'-tetraiodothyronine sodium salt [levothyroxine (T4) sodium]. Synthetic T4 is chemically identical to that produced in the human thyroid gland. Levothyroxine (T4) sodium has an empirical formula of C15H10I4NNaO4 ∙ x H2O (where x = 5), molecular weight of 798.86 g/mol (anhydrous), and structural formula as shown:

TIROSINT (levothyroxine sodium) capsules are amber-colored, round/biconvex capsules containing a viscous amber-colored liquid.

The inactive ingredients in TIROSINT are gelatin, glycerin and water.

12 CLINICAL PHARMACOLOGY

12.1 Mechanism of Action

Thyroid hormones exert their physiologic actions through control of DNA transcription and protein synthesis. Triiodothyronine (T3) and L-thyroxine (T4) diffuse into the cell nucleus and bind to thyroid receptor proteins attached to DNA. This hormone nuclear receptor complex activates gene transcription and synthesis of messenger RNA and cytoplasmic proteins.

The physiological actions of thyroid hormones are produced predominantly by T3, the majority of which (approximately 80%) is derived from T4 by deiodination in peripheral tissues.

12.2 Pharmacodynamics

Oral levothyroxine sodium is a synthetic T4 hormone that exerts the same physiologic effect as endogenous T4, thereby maintaining normal T4 levels when a deficiency is present.

12.3 Pharmacokinetics

Absorption

Absorption of orally administered T4 from the gastrointestinal (GI) tract ranges from 40% to 80%. The majority of the levothyroxine dose is absorbed from the jejunum and upper ileum. T4 absorption is increased by fasting, and decreased in malabsorption syndromes and by certain foods such as soybeans. Dietary fiber decreases the bioavailability of T4. Absorption may also decrease with age. In addition, many drugs and foods affect T4 absorption. [see Drug Interactions (7)]

Distribution

Circulating thyroid hormones are greater than 99% bound to plasma proteins, including thyroxine-binding globulin (TBG), thyroxine-binding prealbumin (TBPA), and thyroxine-binding albumin (TBA), whose capacities and affinities vary for each hormone. The higher affinity of both TBG and TBPA for T4 partially explains the higher serum levels, slower metabolic clearance, and longer half-life of T4 compared to T3. Protein-bound thyroid hormones exist in reverse equilibrium with small amounts of free hormone. Only unbound hormone is metabolically active. Many drugs and physiologic conditions affect the binding of thyroid hormones to serum proteins [see Drug Interactions (7)]. Thyroid hormones do not readily cross the placental barrier [see Use in Specific Populations (8.1)].

Elimination

Metabolism

T4 is slowly eliminated (see Table 6) . The major pathway of thyroid hormone metabolism is through sequential deiodination. Approximately 80% of circulating T3 is derived from peripheral T4 by monodeiodination. The liver is the major site of degradation for both T4 and T3, with T4 deiodination also occurring at a number of additional sites, including the kidney and other tissues. Approximately 80% of the daily dose of T4 is deiodinated to yield equal amounts of T3 and reverse T3 (rT3). T3 and rT3 are further deiodinated to diiodothyronine. Thyroid hormones are also metabolized via conjugation with glucuronides and sulfates and excreted directly into the bile and gut where they undergo enterohepatic recirculation.

Excretion

Thyroid hormones are primarily eliminated by the kidneys. A portion of the conjugated hormone reaches the colon unchanged and is eliminated in the feces. Approximately 20% of T4 is eliminated in the stool. Urinary excretion of T4 decreases with age.

Table 6: Pharmacokinetic Parameters of Thyroid Hormones in Euthyroid Patients
Hormone | Ratio in Thyroglobulin | Biologic Potency | Half-Life (Days) | Protein Binding (%) [Includes TBG, TBPA and TBA.]
Levothyroxine (T4) | 10 – 20 | 1 | 6 – 7 [3 – 4 days in hyperthyroidism, 9 – 10 days in hypothyroidism.] | 99.96
Liothyronine (T3) | 1 | 4 | ≤ 2 | 99.5

13 NONCLINICAL TOXICOLOGY

13.1 Carcinogenesis, Mutagenesis, Impairment of Fertility

Animal studies have not been performed to evaluate the carcinogenic potential, mutagenic potential or effects on fertility of levothyroxine sodium.

16 HOW SUPPLIED/STORAGE AND HANDLING

16.1 How Supplied

TIROSINT (levothyroxine sodium) capsules are amber-colored, round/biconvex capsules, imprinted with a dosage strength specific letter on one side and containing a viscous amber-colored liquid. They are supplied as follows:

Table 7: TIROSINT Packaging Description - Boxes of 30 capsules, consisting of 3 blisters with 10 capsules each
Strength (mcg) | Color [Shown on box and blister packing, not on individual capsules.] | Imprint Code | NDC
13 | Green | A | 71858-0005-4
25 | Orange | E | 71858-0010-4
37.5 | Dark Blue | O | 71858-0012-4
44 | Red | R | 71858-0013-4
50 | White | G | 71858-0015-4
62.5 | Grey | L | 71858-0017-4
75 | Purple | H | 71858-0020-4
88 | Olive | J | 71858-0025-4
100 | Yellow | K | 71858-0030-4
112 | Rose | M | 71858-0035-4
125 | Brown | N | 71858-0040-4
137 | Turquoise | P | 71858-0045-4
150 | Blue | S | 71858-0050-4
175 | Lilac | U | 71858-0055-4
200 | Pink | Y | 71858-0060-4

The dosage strength on each box is clearly identified in several locations, and is associated with a distinct color. The color of the circles on the blister is the same color as on the box. Each blister pack contains 10 capsules placed in individual cavities labeled with the dosage strength and the product name (TIROSINT).

16.2 Storage and Handling

Store at 20°C to 25°C (68°F to 77°F); excursions permitted to 15°-30°C (59-86°F) [see USP Controlled Room Temperature]. TIROSINT capsules should be protected from heat, light and moisture.

Do not separate the individual cavities containing the drug from the intact blister as important information may be lost (i.e., manufacturer/distributor names, distributor contact phone number, lot number, and expiration date), and do not remove the individual capsules from blister packaging until ready to use.

17 PATIENT COUNSELING INFORMATION

Advise the patient and/or the caregiver to read the FDA-approved patient labeling (Patient Information Sheet).

Dosing and Administration

- Instruct patients to take TIROSINT only as directed by their healthcare provider.
- Instruct patients to take TIROSINT one-half to one hour before breakfast.
- Inform patients that agents such as iron and calcium supplements and antacids can decrease the absorption of levothyroxine. Instruct patients not to take TIROSINT within 4 hours of these agents.
- Instruct patients that TIROSINT capsules should be swallowed whole and never be cut, crushed, or chewed.
- To assist with identifying the name and strength of each TIROSINT capsule, instruct patients not to remove capsules from the blisters in advance, particularly if they are taking multiple strengths.
- Instruct patients to notify their healthcare provider should they become pregnant or are thinking of becoming pregnant while taking TIROSINT.

Important Information

- Inform patients that it may take several weeks before they notice an improvement in symptoms.
- Inform patients that the levothyroxine in TIROSINT is intended to replace a hormone that is normally produced by the thyroid gland. Generally, replacement therapy is to be taken for life.
- Inform patients that TIROSINT should not be used as a primary or adjunctive therapy in a weight control program.
- Instruct patients to notify their healthcare provider if they are taking any other medications, including prescription and over-the-counter preparations [see Drug Interactions (7)] .
- Instruct patients to notify their healthcare provider of any other medical conditions, particularly heart disease, diabetes, clotting disorders, and adrenal or pituitary gland problems, as the dose of medications used to control these other conditions may need to be adjusted while taking TIROSINT. If they have diabetes, instruct patients to monitor their blood and/or urinary glucose levels as directed by their physician and immediately report any changes to their physician. If patients are taking anticoagulants, their clotting status should be checked frequently.
- Instruct patients to notify their physician or dentist that they are taking TIROSINT prior to any surgery.

Adverse Reactions

- Instruct patients to notify their healthcare provider if they experience any of the following symptoms: rapid or irregular heartbeat, chest pain, shortness of breath, leg cramps, headache, nervousness, irritability, sleeplessness, tremors, change in appetite, weight loss, vomiting, diarrhea, excessive sweating, heat intolerance, fever, changes in menstrual periods, hives or skin rash, or any other unusual medical event.
- Inform patients that partial hair loss may occur rarely during the first few months of TIROSINT therapy, but this is usually temporary.

Manufactured for IBSA Pharma Inc. by:

IBSA Institut Biochimique SA
6912 Pazzallo
Switzerland

Distributed by:

IBSA Pharma Inc.,
Parsippany, NJ 07054
USA

PATIENT INFORMATION
TIROSINT® [tee-row-sent]
(levothyroxine sodium)
capsules, for oral use

What is the most important information I should know about TIROSINT?

- Do not use TIROSINT to treat weight problems or weight loss.
- Do not take more TIROSINT than your doctor prescribes for you to take. Over dosage or taking too much TIROSINT may cause life-threatening side effects or death.

What is TIROSINT?
TIROSINT is a prescription medicine that contains a hormone called levothyroxine which is normally produced by the thyroid gland. TIROSINT is used to treat adults and children 6 years of age or older:

- to replace or give extra levothyroxine in people whose thyroid does not produce enough of this hormone.
- who need surgery and radioiodine therapy to manage a type of thyroid cancer called thyroid-dependent well-differentiated thyroid cancer.

TIROSINT should not be used to treat people who are recovering from swelling of the thyroid gland (thyroiditis) and whose bodies do not produce enough levothyroxine for a short time.
TIROSINT is unsuitable for children less than 6 years of age or who may be unable to swallow an intact capsule.

Do not take TIROSINT:

- if your adrenal glands are not working well and you have not been treated for this problem.

Before you take TIROSINT, tell your doctor about all of your medical conditions, including if you:

- have or had heart problems.
- have or had thyroid nodules.
- have kidney or pituitary gland problems.
- have any food or drug allergies.
- have a low red blood cell count (anemia).
- have diabetes.
- have weak bones (osteoporosis).
- have or had a history of blood clotting problems.
- have recently received radiation therapy with iodine (such as I-131).
- are pregnant or plan to become pregnant. TIROSINT may harm your unborn baby. Your doctor may need to change your TIROSINT dose while you are pregnant.
- are breastfeeding. TIROSINT can pass into your milk. Talk to your doctor about the best way to feed your baby if you take TIROSINT.

Tell your doctor about all the medicines you take including prescription and over-the-counter medicines, vitamins, and herbal supplements. TIROSINT may affect the way other medicines work, and other medicines may affect how TIROSINT works. You can ask your doctor or pharmacist for a list of medicines that interact with TIROSINT.

How should I take TIROSINT?

- Take TIROSINT exactly as your doctor tells you to take it.
- Your doctor will tell you how much TIROSINT to take each day.
- Swallow TIROSINT capsules whole. Do not cut, crush, or chew TIROSINT capsules before swallowing. If you or your child cannot swallow TIROSINT capsules whole, tell your doctor. You may need a different medicine.
- Your doctor may change your dose, if needed.
- Take your dose of TIROSINT 1 time each day, 30 minutes to 1 hour before breakfast, on an empty stomach.
- Certain medicines can interfere with how TIROSINT is absorbed by your body. Take TIROSINT:
  - at least 4 hours before or after you take medicines that contain calcium carbonate or iron (ferrous sulfate).
  - at least 4 hours before you take medicines that contain bile acid sequestrants or ion exchange resins.
- Know the medicines that you take. Ask your doctor or pharmacist for a list of these medicines, if you are not sure.
- Certain foods including soybean flour, cotton seed meal, walnuts, and dietary fiber can affect your treatment and dose of TIROSINT. Talk to your doctor if you eat or drink these foods.
- Do not remove TIROSINT capsules from the original blister package until you are ready to take them.
- Your doctor should do certain blood tests while you are taking TIROSINT and may change your daily dose of TIROSINT as needed. You should not stop taking TIROSINT or change your dose unless your doctor tells you to.
- It may take weeks before you notice your symptoms getting better. Keep using this medicine even if you feel well.
- If you take too much TIROSINT or overdose, call your doctor or poison control center at 1-800-222-1222, or go to the nearest hospital emergency room right away.

What are the possible side effects of TIROSINT?
TIROSINT may cause serious side effects, including:

- heart problems. You may experience an increased heart rate, chest pain and irregular heartbeat. Your risk of developing heart problems may be greater if you are elderly, have heart problems, or if you take too much TIROSINT. Your doctor may reduce your dose or stop treatment with TIROSINT for a while if you develop heart problems.
- worsening diabetic control. If you are diabetic, it may be harder to control your blood sugar levels causing hyperglycemia while taking TIROSINT. Check your blood sugar levels closely after starting, changing, or stopping treatment with TIROSINT. Your doctor may have to change your diabetes treatment plan.
- weak or brittle bones. Your risk of developing weak or brittle bones may be greater if you are post-menopausal or you take too much TIROSINT.

The most common side effects of TIROSINT include:

- irregular heartbeat
- chest pain
- shortness of breath
- leg cramps
- headache
- nervousness
- hives or skin rash

- irritability
- sleep problems (insomnia)
- tremors
- muscle weakness
- change in appetite
- weight loss

- vomiting
- diarrhea
- sweating a lot
- heat intolerance
- fever
- changes in menstrual period

Other side effects may include:

- partial hair loss during the first months of treatment with TIROSINT. This usually lasts a short period of time (temporary).

These are not all the possible side effects of TIROSINT. Call your doctor for medical advice about side effects. You may report side effects to FDA at 1-800-FDA-1088.
You may also report side effects to IBSA Pharma Inc. at 1-800-587-3513 or www.fda.gov/medwatch.

How should I store TIROSINT?

- Store TIROSINT at room temperature between 68°F to 77°F (20°C to 25°C).
- Store TIROSINT away from heat, light, and moisture.
- Keep TIROSINT in the original blister pack until you are ready to use it.

Keep TIROSINT and all medicines out of the reach of children.

General information about the safe and effective use of TIROSINT
Medicines are sometimes prescribed for purposes other than those listed in a Patient Information leaflet. Do not use TIROSINT for a condition for which it was not prescribed. Do not give TIROSINT to other people, even if they have the same symptoms that you have. It may harm them. You can ask your pharmacist or doctor for information about TIROSINT that is written for health professionals.

What are the ingredients in TIROSINT?
Active ingredient : levothyroxine sodium
Inactive ingredients: gelatin, glycerin, and water
Manufactured by: IBSA Institut Biochimique SA, 6912 Pazzallo, Switzerland;
Marketed and distributed by: IBSA Pharma Inc., Parsippany, NJ 07054 USA
For more information, go to www.tirosint.com or call 1-800-587-3513.

This Patient Information has been approved by the U.S. Food and Drug Administration

Issued: October 2022

PRINCIPAL DISPLAY PANEL - 13 mcg Capsule Blister Pack Carton

TIROSINT®
(levothyroxine sodium) capsules

NDC 71858-0005-4

13 mcg
per capsule

Do not remove individual capsules from blister packaging until ready to use

Swallow capsule whole. Do not cut, crush, or chew.

Rx Only
3 blisters x 10 capsules

IBSA

PRINCIPAL DISPLAY PANEL - 25 mcg Capsule Blister Pack Carton

TIROSINT®
(levothyroxine sodium) capsules

NDC 71858-0010-4

25 mcg per capsule

Do not remove individual capsules from blister packaging until ready to use

Swallow capsule whole. Do not cut, crush, or chew.

Rx Only
3 blisters x 10 capsules

IBSA

PRINCIPAL DISPLAY PANEL - 37.5 mcg Capsule Blister Pack Carton

TIROSINT ®
(levothyroxine sodium) capsules

NDC 71858-0012-4

37.5 mcg per capsule

Do not remove individual capsules from blister packaging until ready to use

Swallow capsule whole. Do not cut, crush, or chew.

R x Only
3 blisters x 10 capsules

IBSA

PRINCIPAL DISPLAY PANEL - 44 mcg Capsule Blister Pack Carton

TIROSINT ®
(levothyroxine sodium) capsules

NDC 71858-0013-4

44 mcg per capsule

Do not remove individual capsules from blister packaging until ready to use

Swallow capsule whole. Do not cut, crush, or chew.

R x Only
3 blisters x 10 capsules

IBSA

PRINCIPAL DISPLAY PANEL - 50 mcg Capsule Blister Pack Carton

TIROSINT®
(levothyroxine sodium) capsules

NDC 71858-0015-4

50 mcg per capsule

Do not remove individual capsules from blister packaging until ready to use

Swallow capsule whole. Do not cut, crush, or chew.

Rx Only
3 blisters x 10 capsules

IBSA

PRINCIPAL DISPLAY PANEL - 62.5 mcg Capsule Blister Pack Carton

TIROSINT ®
(levothyroxine sodium) capsules

NDC 71858-0017-4

62.5 mcg per capsule

Do not remove individual capsules from blister packaging until ready to use

Swallow capsule whole. Do not cut, crush, or chew.

R x Only
3 blisters x 10 capsules

IBSA

PRINCIPAL DISPLAY PANEL - 75 mcg Capsule Blister Pack Carton

TIROSINT®
(levothyroxine sodium) capsules

NDC 71858-0020-4

75 mcg per capsule

Do not remove individual capsules from blister packaging until ready to use

Swallow capsule whole. Do not cut, crush, or chew.

Rx Only
3 blisters x 10 capsules

IBSA

PRINCIPAL DISPLAY PANEL - 88 mcg Capsule Blister Pack Carton

TIROSINT®
(levothyroxine sodium) capsules

NDC 71858-0025-4

88 mcg per capsule

Do not remove individual capsules from blister packaging until ready to use

Swallow capsule whole. Do not cut, crush, or chew.

Rx Only
3 blisters x 10 capsules

IBSA

PRINCIPAL DISPLAY PANEL - 100 mcg Capsule Blister Pack Carton

TIROSINT®
(levothyroxine sodium) capsules

NDC 71858-0030-4

100 mcg per capsule

Do not remove individual capsules from blister packaging until ready to use

Swallow capsule whole. Do not cut, crush, or chew.

Rx Only
3 blisters x 10 capsules

IBSA

PRINCIPAL DISPLAY PANEL - 112 mcg Capsule Blister Pack Carton

TIROSINT®
(levothyroxine sodium) capsules

NDC 71858-0035-4

112 mcg per capsule

Do not remove individual capsules from blister packaging until ready to use

Swallow capsule whole. Do not cut, crush, or chew.

Rx Only
3 blisters x 10 capsules

IBSA

PRINCIPAL DISPLAY PANEL - 125 mcg Capsule Blister Pack Carton

TIROSINT®
(levothyroxine sodium) capsules

NDC 71858-0040-4

125 mcg per capsule

Do not remove individual capsules from blister packaging until ready to use

Swallow capsule whole. Do not cut, crush, or chew.

Rx Only
3 blisters x 10 capsules

IBSA

PRINCIPAL DISPLAY PANEL - 137 mcg Capsule Blister Pack Carton

TIROSINT®
(levothyroxine sodium) capsules

NDC 71858-0045-4

137 mcg per capsule

Do not remove individual capsules from blister packaging until ready to use

Swallow capsule whole. Do not cut, crush, or chew.

Rx Only
3 blisters x 10 capsules

IBSA

PRINCIPAL DISPLAY PANEL - 150 mcg Capsule Blister Pack Carton

TIROSINT®
(levothyroxine sodium) capsules

NDC 71858-0050-4

150 mcg per capsule

Do not remove individual capsules from blister packaging until ready to use

Swallow capsule whole. Do not cut, crush, or chew.

Rx Only
3 blisters x 10 capsules

IBSA

PRINCIPAL DISPLAY PANEL - 175 mcg Capsule Blister Pack Carton

TIROSINT®
(levothyroxine sodium) capsules

NDC 71858-0055-4

175 mcg per capsule

Do not remove individual capsules from blister packaging until ready to use

Swallow capsule whole. Do not cut, crush, or chew.

Rx Only
3 blisters x 10 capsules

IBSA

PRINCIPAL DISPLAY PANEL - 200 mcg Capsule Blister Pack Carton

TIROSINT®
(levothyroxine sodium) capsules

NDC 71858-0060-4

200 mcg per capsule

Do not remove individual capsules from blister packaging until ready to use

Swallow capsule whole. Do not cut, crush, or chew.

Rx Only
3 blisters x 10 capsules

IBSA